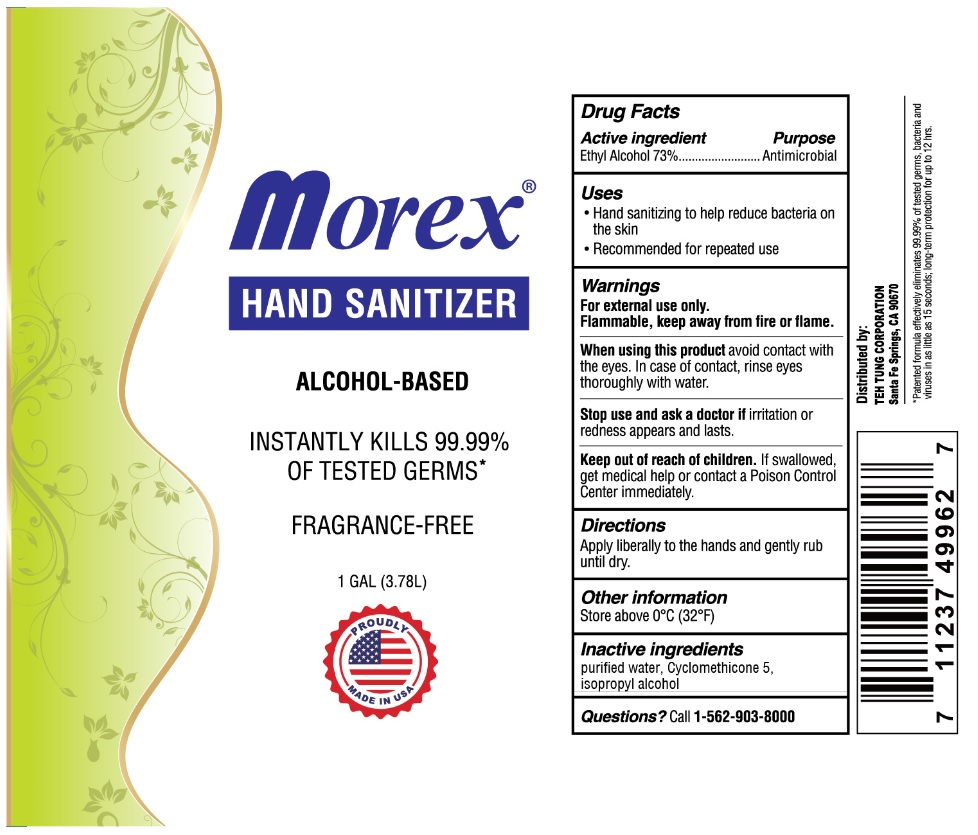 DRUG LABEL: Morex
NDC: 78168-828 | Form: LIQUID
Manufacturer: Teh Tung Corporation
Category: otc | Type: HUMAN OTC DRUG LABEL
Date: 20200615

ACTIVE INGREDIENTS: ALCOHOL 73 mL/100 mL
INACTIVE INGREDIENTS: WATER; CYCLOMETHICONE 5; ISOPROPYL ALCOHOL

morex® HAND SANITIZER

Active ingredient

Ethyl Alcohol 73%

Purpose

Antimicrobial

Uses

- Hand sanitizing to help reduce bacteria on the skin
- Recommended for repeated use

Warnings

For external use only.

Flammable, keep away from fire or flame.

When using this product avoid contact with the eyes. In case of contact, rinse eyes thoroughly with water.

Stop use and ask a doctor if irritation or redness appears and lasts.

Keep out of reach of children. If swallowed, get medical help or contact a Poison Control Center immediately.

Directions

Apply liberally to the hands and gently rub until dry.

Other information

Store above 0°C (32°F)

Inactive ingredients

purified water, cyclomethicone 5, isopropyl alcohol

Questions? Call 1-562-903-8000

ALCOHOL-BASED

INSTANTLY KILLS 99.99% OF TESTED GERMS

FRAGRANCE -FREE

PROUDLY MADE IN USA

Distributed by:

TEH TUNG CORPORATION

Santa Fe Springs, CA 90670

*Patents formula effectively eliminates 99.99% of tested germs, bacteria and viruses in as little as 15 seconds; long-term protection for up to 12 hrs.